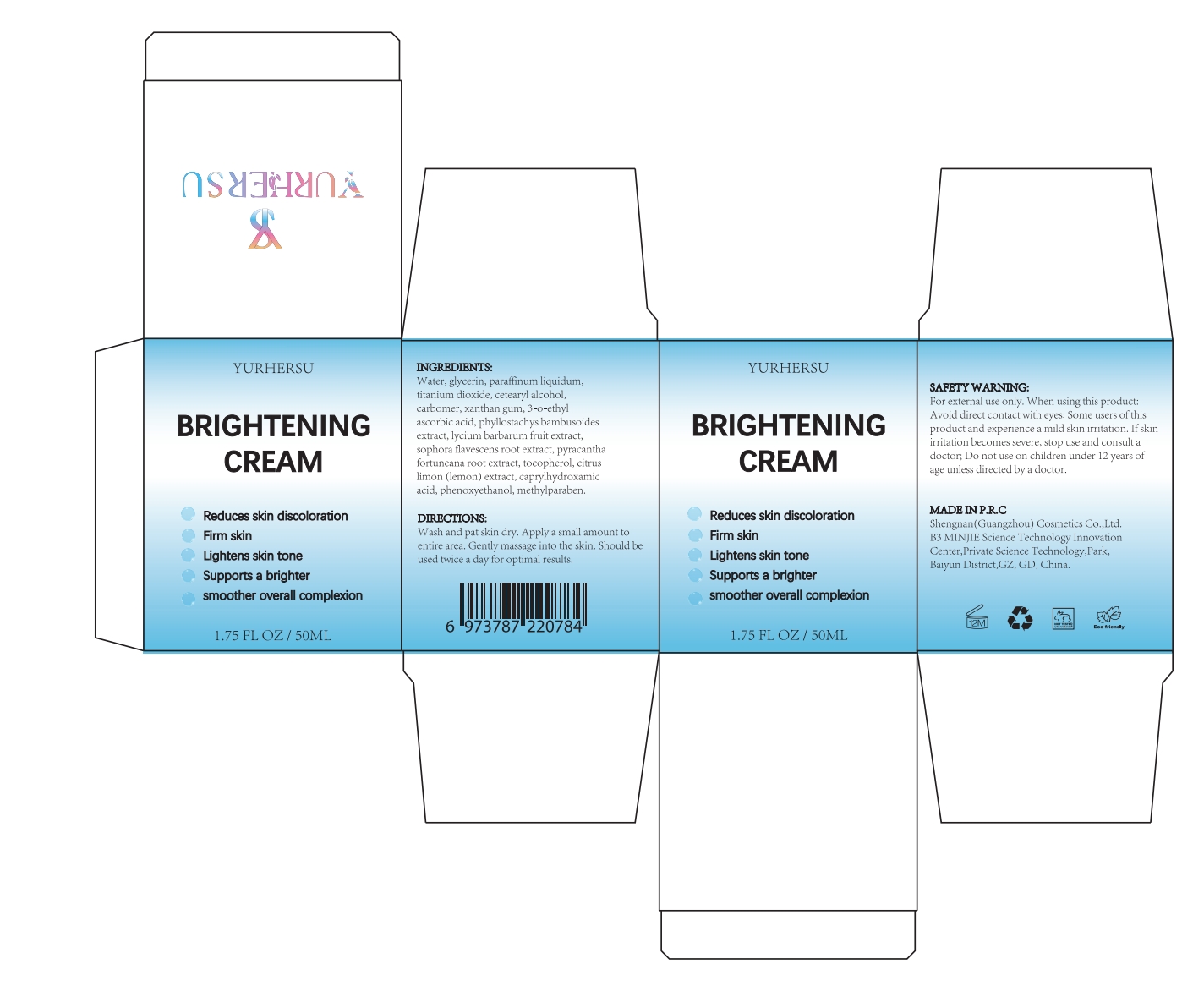 DRUG LABEL: Brightening Gream
NDC: 84019-005 | Form: LOTION
Manufacturer: Shengnan (Guangzhou) Cosmetics Co.,LTD
Category: otc | Type: HUMAN OTC DRUG LABEL
Date: 20240702

ACTIVE INGREDIENTS: 3-O-ETHYL ASCORBIC ACID 100 mg/1 g
INACTIVE INGREDIENTS: PHENOXYETHANOL; TITANIUM DIOXIDE; XANTHAN GUM; CARBOMER 980; CAPRYLHYDROXAMIC ACID; METHYLPARABEN; WATER; TOCOPHEROL; GLYCERIN

BRIGHTENING CREAM

Active ingredients

3-o-ethyl ascorbic acid 1%

Purpose

Whitening Cream

WARNINGS

For external use only, When using this product:Avoid direct contact with eyes, Some users ofthisproduct and experience a mild skin irritation. Ifskinirritation becomes severe, stop use and consult adoctor, Do not use on children under 12 years ofage unless directed by a doctor.

Stop use and ask a doctor if

rash occurs

Do not use

on damaged or broken skin

When using this product

keep out of eyes. Rinse with water to remove.

Keep out of reach of children.

If swallowed, get medical heip or contact a Poison Control Center right away.

INACTIVE INGREDIENT

water 74.75%
glycerin 8%
paraffinum liquidum 8%

titanium dioxide 2%

cetearyl alcohol 2.5%

carbomer 0.2%

xanthan gum 0.5%

phyllostachys bambusoides extract 1%

lycium barbarum fruit extract 0.3%

sophora flavescens root extract 0.3%

Pyracantha fortuneana root extract 0.3%

tocopherol 0.5%

citruslimon (lemon)extract 0.2%

caprylhydroxamicacid 0.05%

phenoxyethanol 0.2%

methylparaben 0.2%

DOSAGE

Once a day, do not rinse with cold water within 2 hours after use.

INDICATIONS AND USAGE

Helps reduce pigmentation on the skin, making the skin tone more even.Whitening cream is suitable for facial skin and can be applied evenly or topically throughout the entire face.